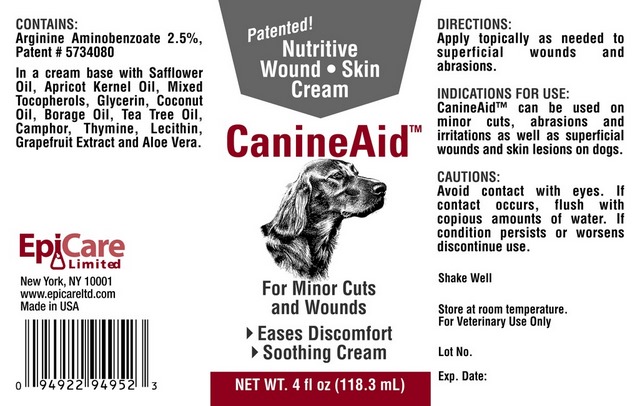 DRUG LABEL: CanineAid
NDC: 67113-002 | Form: CREAM
Manufacturer: EpiCare Limited
Category: animal | Type: OTC ANIMAL DRUG LABEL
Date: 20100901

ACTIVE INGREDIENTS: ARGININE 2.25 g/118.3 mL; AMINOBENZOIC ACID 0.7 g/118.3 mL
INACTIVE INGREDIENTS: SAFFLOWER OIL; APRICOT SEED OIL; ALPHA-TOCOPHEROL; GLYCERIN; COCONUT OIL; BORAGE OIL; TEA TREE OIL; CAMPHOR OIL; THYMINE; LECITHIN, SOYBEAN; CITRUS PARADISI SEED; ALOE VERA LEAF

DESCRIPTION

Nutritive Wound - Skin Cream
For Minor Cuts and Wounds
- Eases Discomfort
- Soothing Cream

VETERINARY INDICATIONS

CONTAINS:

Arginine Aminobenzoate 2.5% Patent # 5734080

In a cream base with Safflower Oil, Apricot Kernel Oil, Mixed Tocopherols, Glycerin, Coconut Oil, Borage Oil, Tea Tree Oil, Camphor, Thymine, Lecithin, Grapefruit Extract and Aloe Vera.

DIRECTIONS:

Apply topically as needed to superficial wounds and abrasions.

INDICATIONS FOR USE:

CanineAid can be used on minor cuts, abrasions and irritations as well as superficial wounds and skin lesions on dogs.

PRECAUTIONS

CAUTIONS:

Avoid contact with eyes. If contact occurs, flush with copious amounts of water. If condition persists or worsens discontinue use.

Shake Well

Store at room temperature.

For Veterinary Use Only

Principal Display Panel - 16 fl oz (473.1 mL)

Patented!

Nutritive Wound - Skin Cream

CanineAid

For Minor Cuts and Wounds

- Eases Discomfort

- Soothing Cream

NET WT. 4 fl oz (118.3 mL)